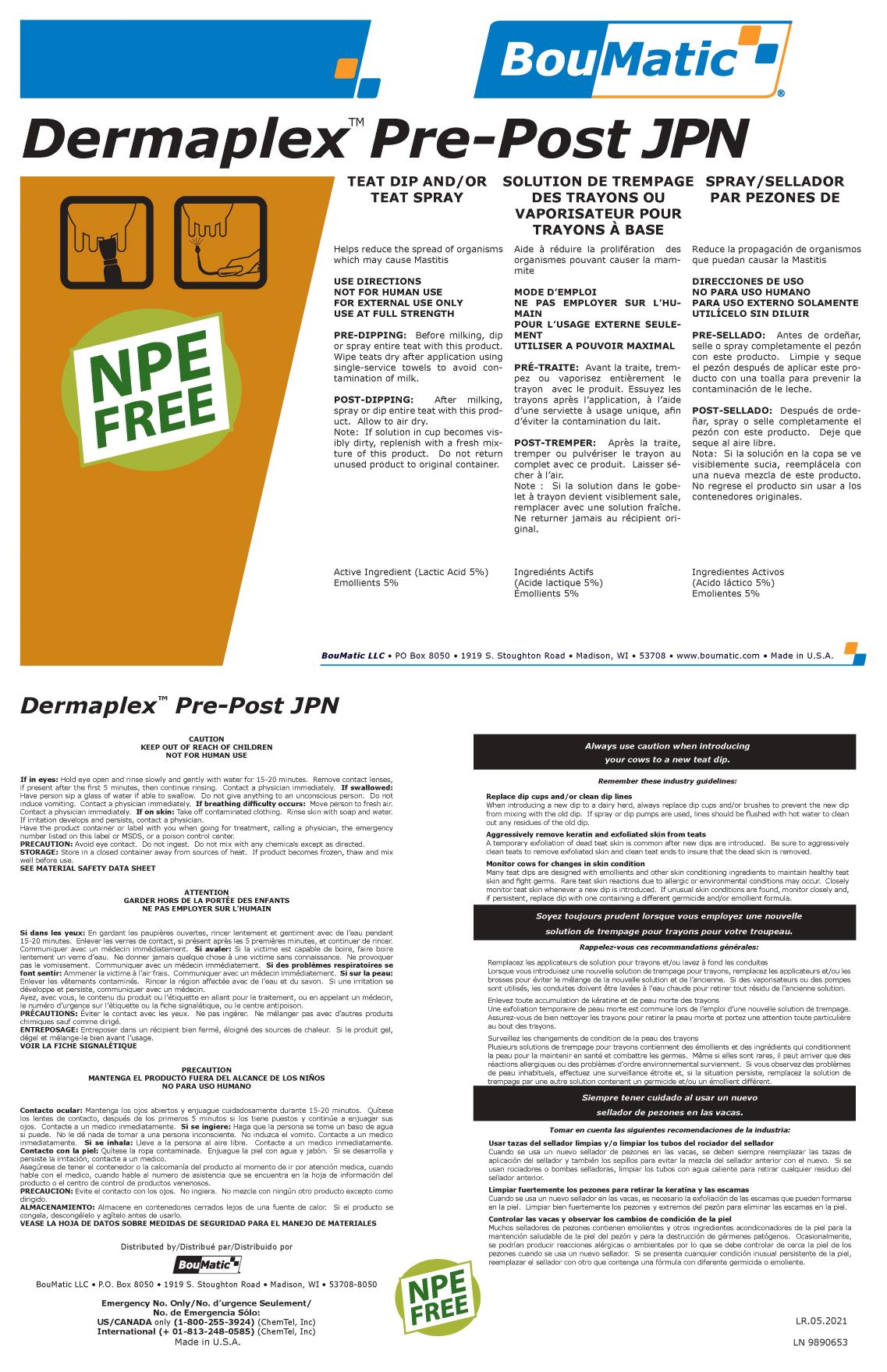 DRUG LABEL: Dermaplex PrePost JPN
NDC: 48106-2042 | Form: LIQUID
Manufacturer: BouMatic, LLC
Category: animal | Type: OTC ANIMAL DRUG LABEL
Date: 20210526

ACTIVE INGREDIENTS: LACTIC ACID 5.68 g/100 g
INACTIVE INGREDIENTS: WATER 85.82 g/100 g; SORBITOL 2 g/100 g; GLYCERIN 3 g/100 g; DODECYL BENZENE SULFONATE DIETHANOLAMINE (MIXED ISOMERS) 1.5 g/100 g; SODIUM HYDROXIDE 2 g/100 g

Dermaplex PrePost JPN

USE DIRECTIONS

NOT FOR HUMAN USE
FOR EXTERNAL USE ONLY
USE AT FULL STRENGTH

FIRST AID:
If in eyes: Hold eye open and rinse slowly and gently with water for 15-20 minutes. Remove contact lenses,
if present after the first 5 minutes, then continue rinsing. Contact a physician immediately. If swallowed:
Have person sip a glass of water if able to swallow. Do not give anything to an unconscious person. Do not
induce vomiting. Contact a physician immediately. If breathing difficulty occurs: Move person to fresh air.
Contact a physician immediately. If on skin: Take off contaminated clothing. Rinse skin with soap and water.
If irritation develops and persists, contact a physician.
Have the product container or label with you when going for treatment, calling a physician, the emergency
number listed on this label or MSDS, or a poison control center.

Storage:

Store in a closed container away from sources of heat. If product becomes frozen, thaw and mix
well before use.

PRE-DIPPING AND POST-DIPPING INSTRUCTIONS

PRE-DIPPING: BEFORE MILKING, DIP OR SPRAY ENTIRE TEAT WITH THIS PRODUCT. WIPE TEATS DRY AFTER APPLICATION USING SINGLE-SERVICE TOWELS TO AVOID CONTAMINATIN OF MILK.

POST-DIPPING: AFTER MILKING, SPRAY OR DIP ENTIRE TEAT WITH THIS PRODUCT. ALLOW TO AIR DRY.

NOTE: IF SOLUTION IN CUP BECOMES VISIBLY DIRTY, REPLENISH WITH A FRESH MIXTURE OF THIS PRODUCT. DO NOT RETURN UNUSED PRODUCT TO ORIGINAL CONTAINER.

Dermaplex PrePost JPN label (Revised 6/2/21)